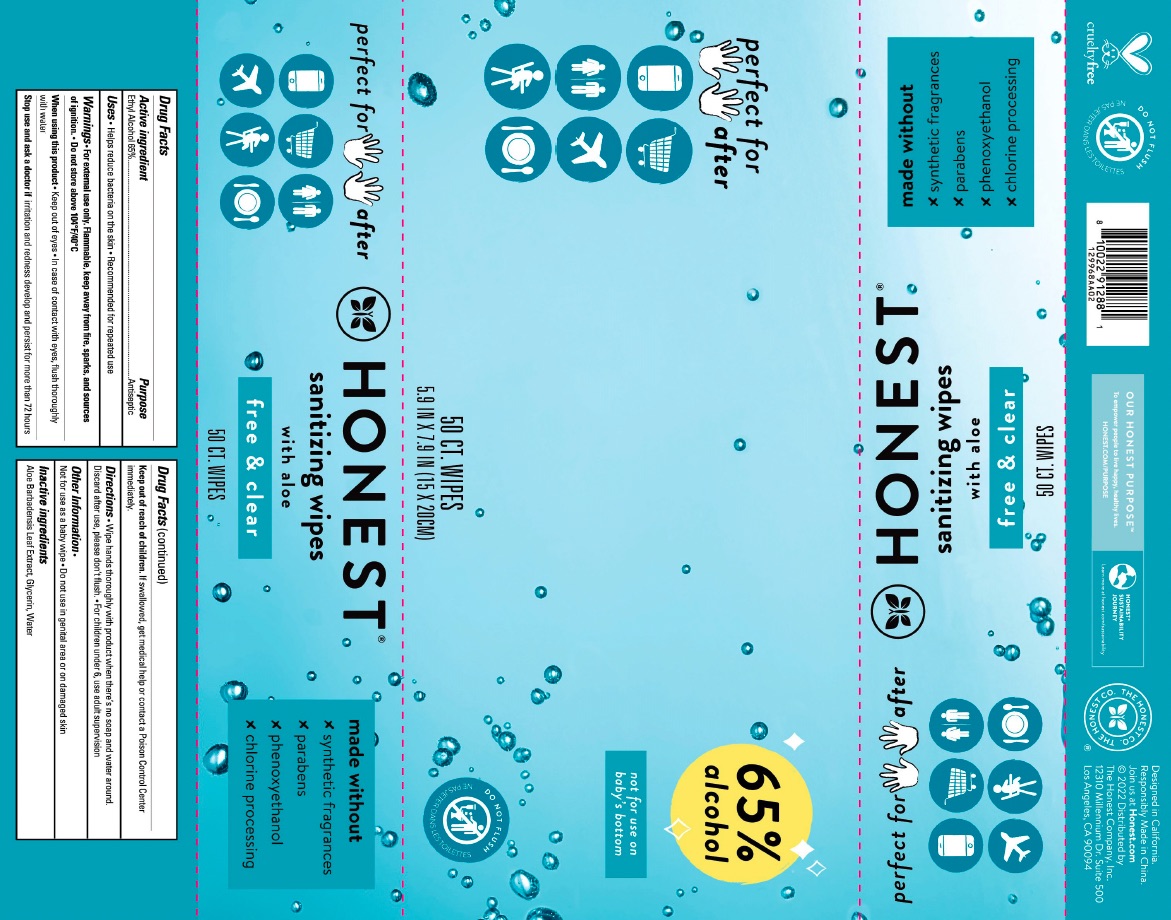 DRUG LABEL: Sanitizing Wipes Fragrance Free
NDC: 69366-316 | Form: CLOTH
Manufacturer: The Honest Company
Category: otc | Type: HUMAN OTC DRUG LABEL
Date: 20231219

ACTIVE INGREDIENTS: ALCOHOL 65 mL/100 mL
INACTIVE INGREDIENTS: ALOE VERA LEAF; GLYCERIN; WATER

Sanitizing Wipes Fragrance Free

ACTIVE INGREDIENT

Ethyl Alcohol 65%

PURPOSE

Antiseptic

Uses

Helps reduce bacteria on the skin

Recommended for repeated use

WARNINGS

For external use only. Flammable, Keep away from the fire, sparks, and sources of ignition

Do not store above 104F/40C

WHEN USING

Keep out of eyes

Incase of contact with eyes, flush thoroughly with water

Stop use and ask a doctor if

irritation and redness develop and persist for more than 72 hours

KEEP OUT OF REACH OF CHILDREN

if swallowed, get medical help or contact a Poison Control Center immediately

Other Information

Not for use as a baby wipe

Do not use in genital area or on damaged skin

Directions

Wipe hands thoroughly with product when there's no soap and water around.

Discard after use, please don't flush

For children under 6, use adult supervision

INACTIVE INGREDIENT

Aloe Barbadensis Leaf Extract, Glycerin, Water